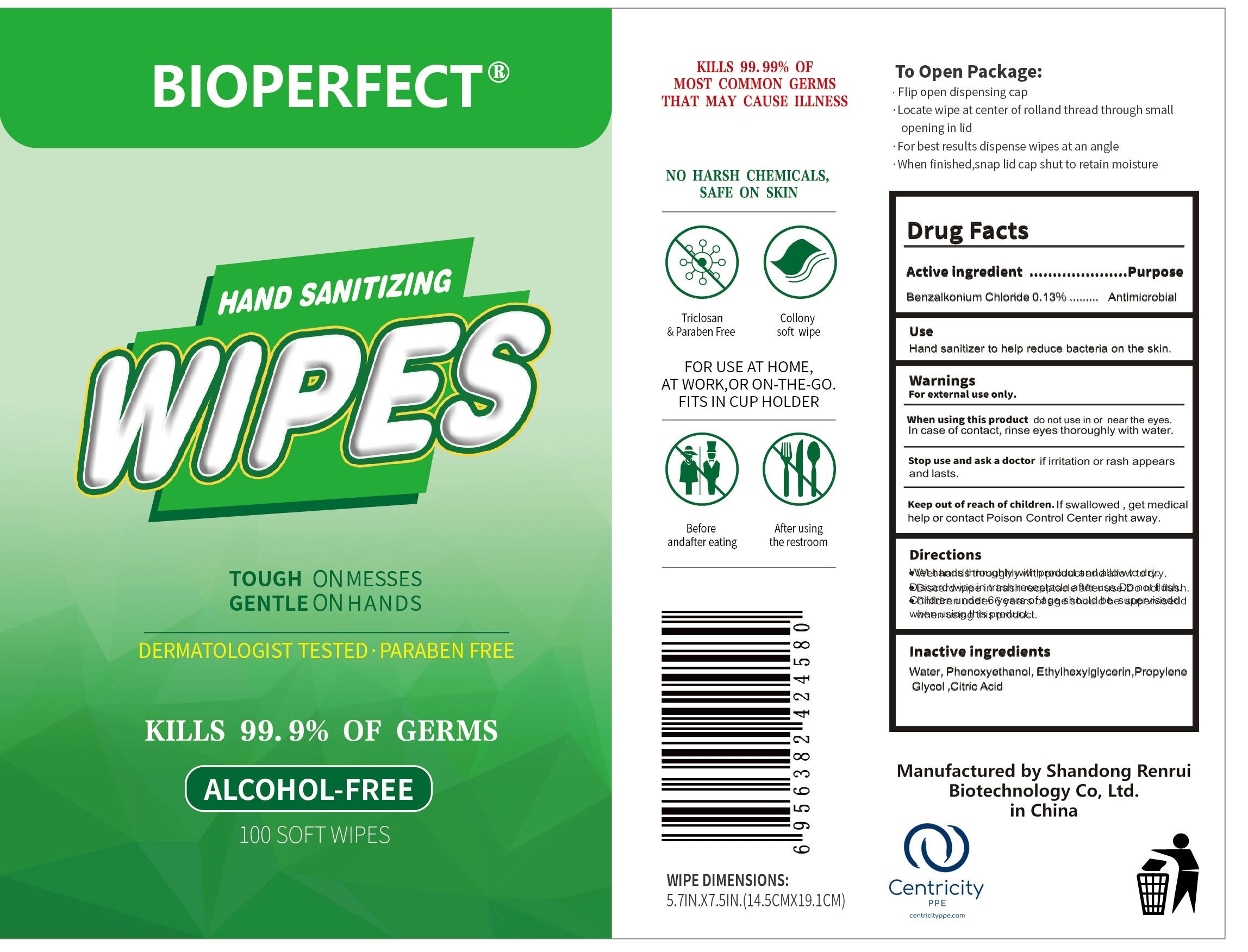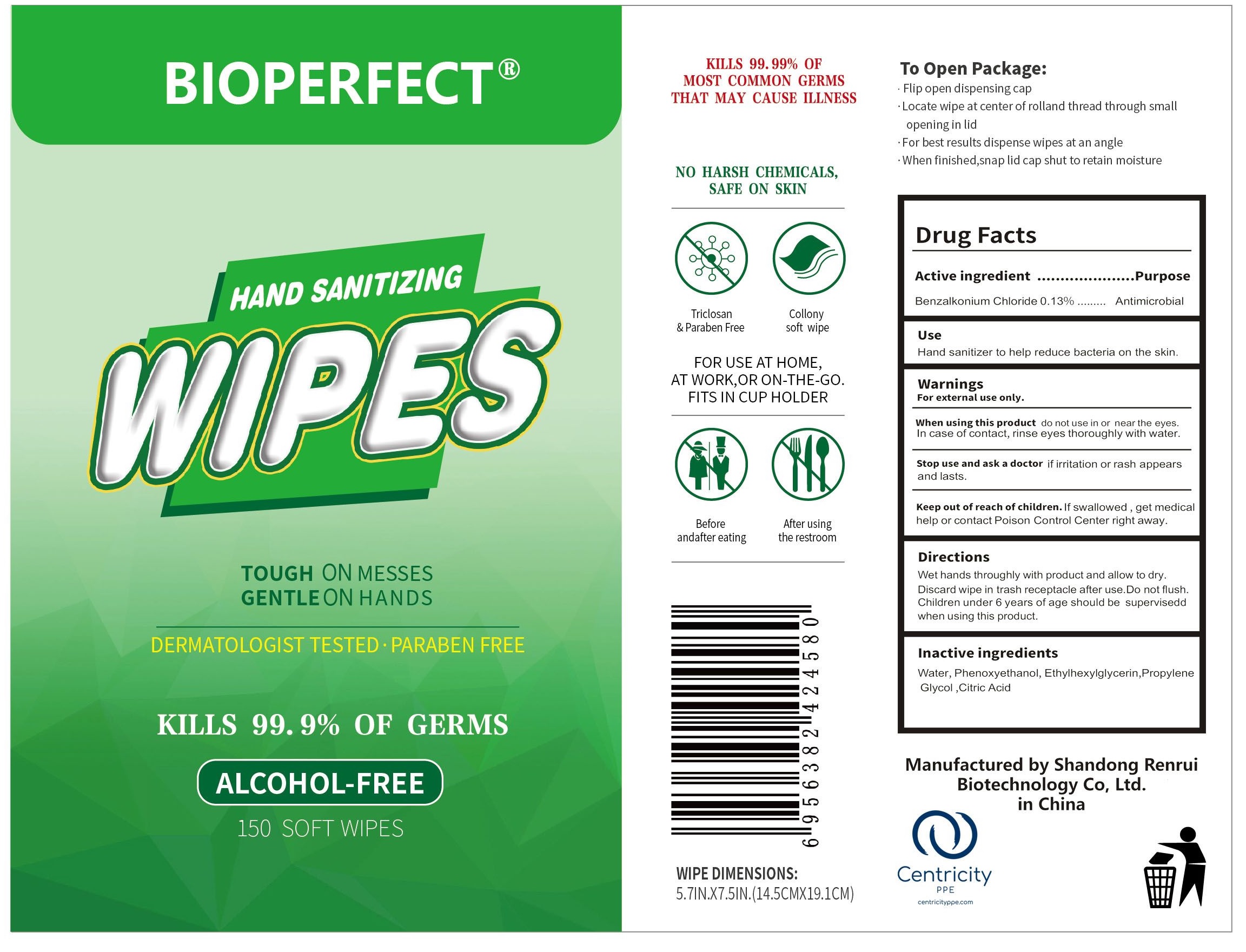 DRUG LABEL: BIOPERFECT Hand Sanitizing Wipes (Alcohol Free)
NDC: 77985-003 | Form: CLOTH
Manufacturer: Shandong Renrui Biotechnology Co, Ltd.
Category: otc | Type: HUMAN OTC DRUG LABEL
Date: 20200828

ACTIVE INGREDIENTS: BENZALKONIUM CHLORIDE 1.3 mg/1 mL
INACTIVE INGREDIENTS: WATER; PHENOXYETHANOL; ETHYLHEXYLGLYCERIN; PROPYLENE GLYCOL; CITRIC ACID MONOHYDRATE

BIOPERFECT Hand Sanitizing Wipes (Alcohol Free)

Active ingredient

Benzalkonium Chloride 0.13%

Purpose

Antimicrobial

Use

Hand sanitizing to help reduce bacteria on the skin.

Warnings

For external use only.

When using this product

do not use in or near the eyes. In case of contact, rinse eyes thoroughly with water.

Stop use and ask a doctor

if irritation or rash appears and lasts.

Keep out of reach of children.

If swallowed, get medical help or contact Poison Control Center right away.

Directions

Wet hands thoroughly with product and allow to dry. Discard wipe in trash receptacle after use. Do not flush. Children under 6 years of age should be supervised when using this product.

Inactive ingredients

Water, Phenoxyethanol, Ethylglycerin, Propylene Glycol,Citric Acid